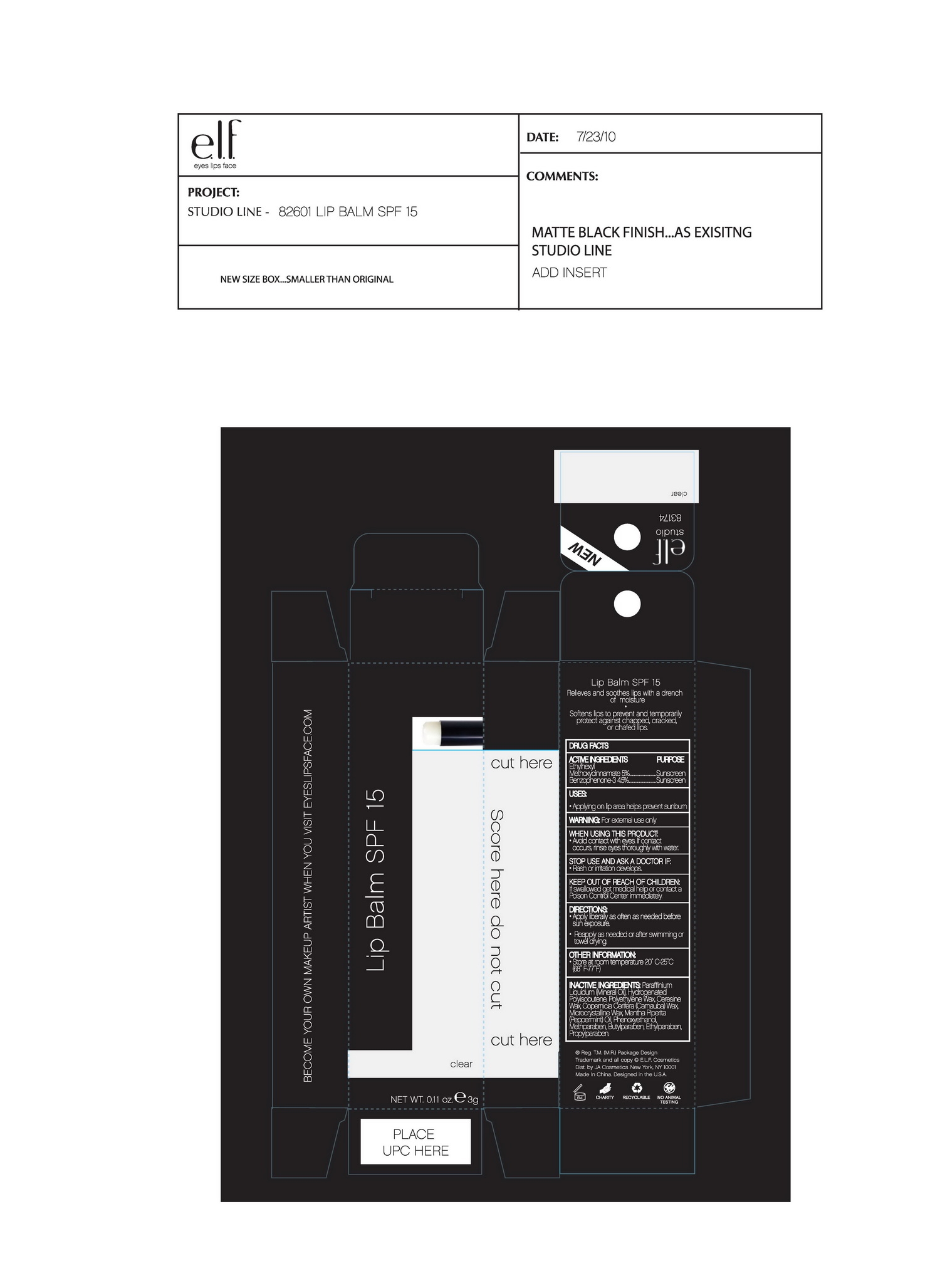 DRUG LABEL: ELF Lip Balm SPF 15
NDC: 52664-008 | Form: CREAM
Manufacturer: Hangzhou Facecare Cosmetics Co., Ltd.
Category: otc | Type: HUMAN OTC DRUG LABEL
Date: 20101117

ACTIVE INGREDIENTS: OXYBENZONE 4.5 g/100 g; OCTINOXATE 5 g/100 g
INACTIVE INGREDIENTS: POLYISOBUTYLENE (1200000 MW); CARNAUBA WAX; MICROCRYSTALLINE WAX; METHYLPARABEN; PROPYLPARABEN; LIGHT MINERAL OIL 39.8 g/100 g; PEPPERMINT OIL; PHENOXYETHANOL; ETHYLPARABEN; BUTYLPARABEN

Drug Fact

Active Ingredient:

Benzophenone-3: 4.5%

Ethylhexyl Methoxycinnamate: 5.0%

Purpose:

Sunscreen

Uses:

Applying on lip area helps prevent sunburn

Warning:

For external use only

When Using This Product:

Avoid contact with eyes. If contact occurs rinse eyes thoroughly with water

Stop Use and Ask A Doctor If:

Rash or irritation develops and lasts

Keep Out Of Reach Of Children:

If swallowed get medical help or contact a Poison Control Center immediately

Directions:

Apply liberally as often as needed before sun exposure.

Reapply as needed or after swimming or towel drying

Other Information
Store at room temperature 20-25 C (77-86F)

Inactive Ingredient:

Paraffinium Liquidum (Mineral Oil), hydrogenated Polyisobutene, Polyethylene Wax, Ceresine Wax, Copernicia Cerifera (Carnauba) Wax, Microcrystalline Wax, Mentha Piperita (Peppermint) Oil, Phenoxyethanol, Methylparaben, Butylparaben, Ethylparaben, Propylparaben.

PACKAGE LABEL

labe